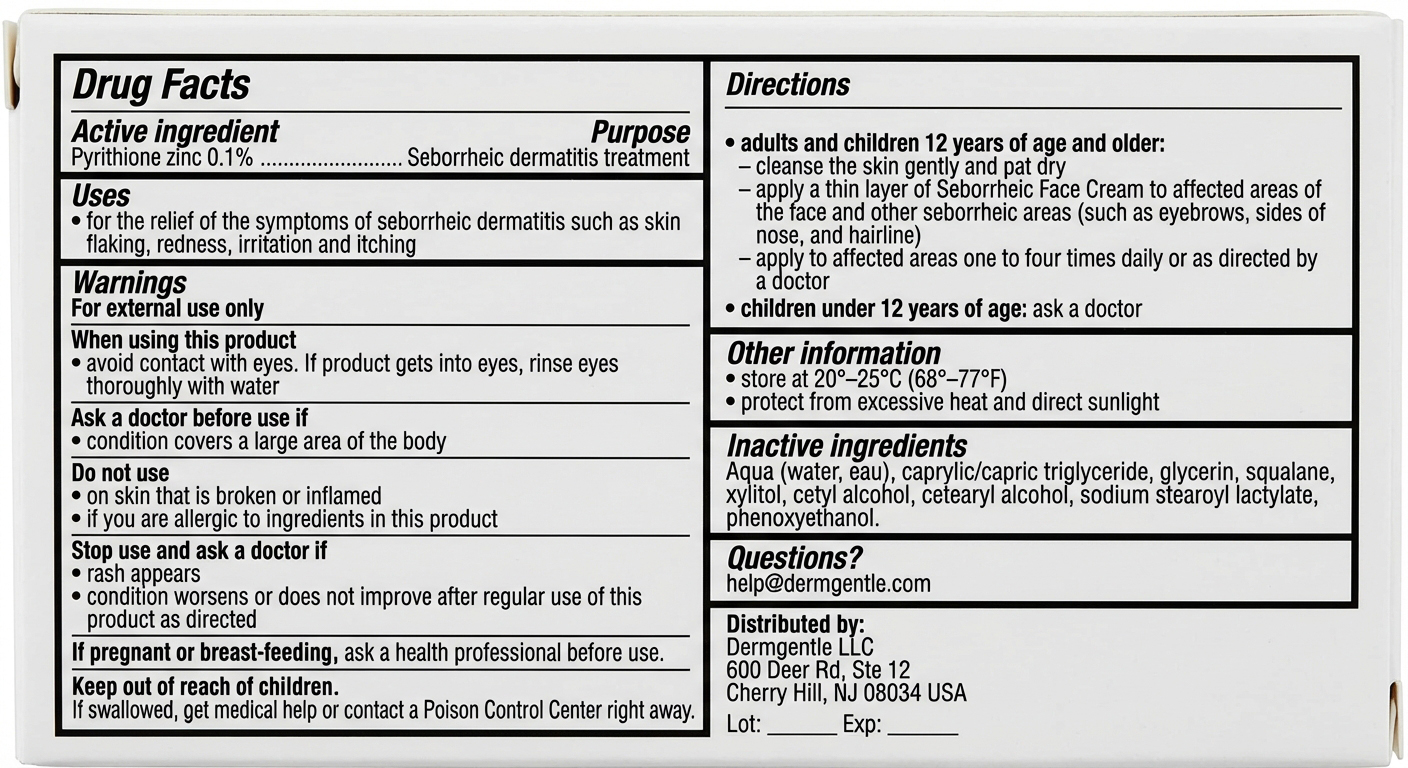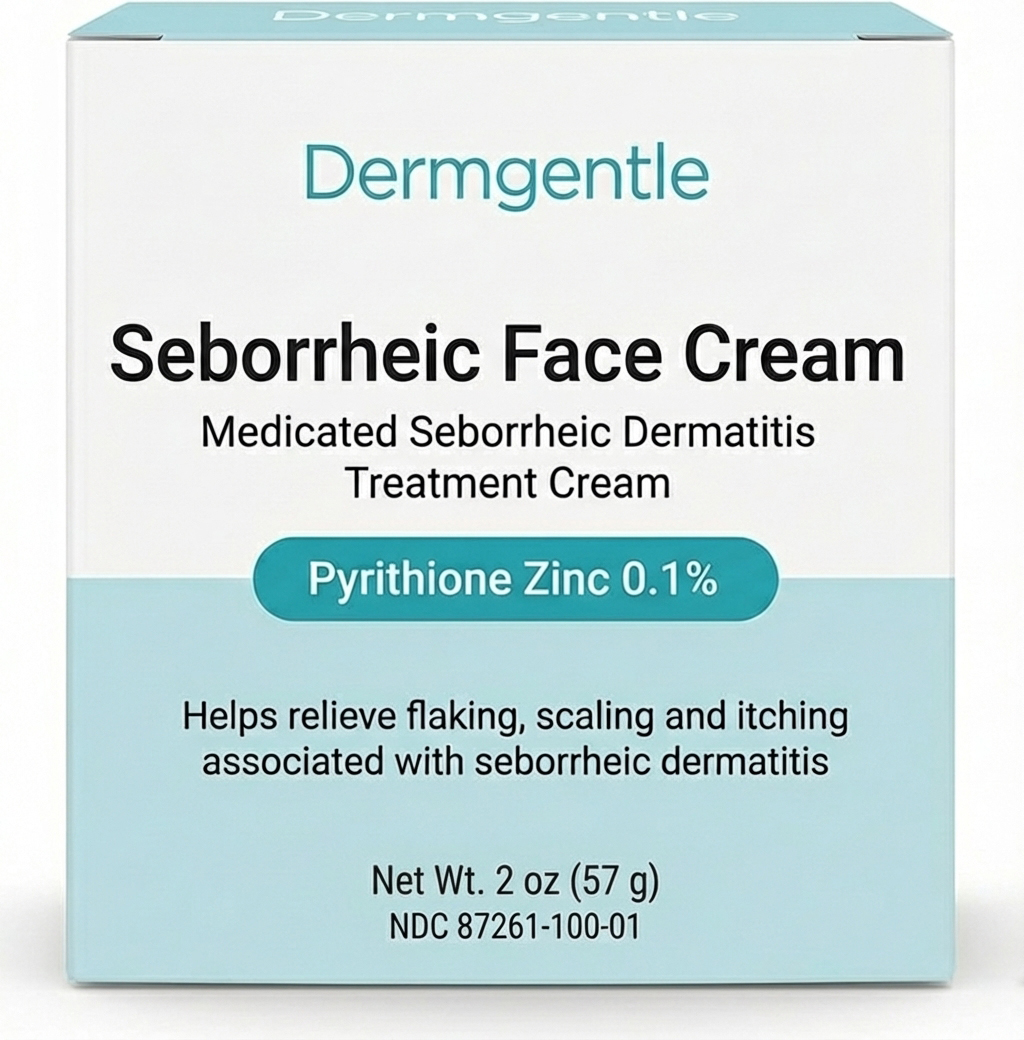 DRUG LABEL: Dermgentle Seborrheic Face Cream
NDC: 87261-100 | Form: CREAM
Manufacturer: Dermgentle LLC
Category: otc | Type: HUMAN OTC DRUG LABEL
Date: 20251212

ACTIVE INGREDIENTS: PYRITHIONE ZINC 1 mg/1 g
INACTIVE INGREDIENTS: SQUALANE; GLYCERIN; SODIUM STEAROYL LACTYLATE; CETYL ALCOHOL; CETEARYL ALCOHOL; PHENOXYETHANOL; AQUA; XYLITOL; CAPRYLIC/CAPRIC TRIGLYCERIDE

Seborrheic Face Cream

Indications and usage

For the relief of the symptoms of seborrheic dermatitis such as skin flaking, redness, irritation and itching.

Dosage and administration

Adults and children 12 years of age and older:

• cleanse the skin gently and pat dry

• apply a thin layer of Seborrheic Face Cream to affected areas of the face and other seborrheic areas (such as eyebrows, sides of nose, and hairline)

• apply to affected areas one to four times daily or as directed by a doctor

Children under 12 years of age: ask a doctor.

Warnings

For external use only.

When using this product

• avoid contact with eyes. If product gets into eyes, rinse eyes thoroughly with water.

Ask a doctor before use if

• condition covers a large area of the body.

Do not use

• on skin that is broken or inflamed

• if you are allergic to ingredients in this product.

Stop use and ask a doctor if

• rash appears

• condition worsens or does not improve after regular use of this product as directed.

If pregnant or breast-feeding, ask a health professional before use.

Inactive ingredients

Aqua (water, eau), caprylic/capric triglyceride, glycerin, squalane, xylitol, cetyl alcohol, cetearyl alcohol, sodium stearoyl lactylate, phenoxyethanol.

Purpose

Seborrheic dermatitis treatment.

Keep out of reach of children. If swallowed, get medical help or contact a Poison Control Center right away.

Principal display panel and Drug Facts labeling for Dermgentle Seborrheic Face Cream (Pyrithione zinc 0.1%).